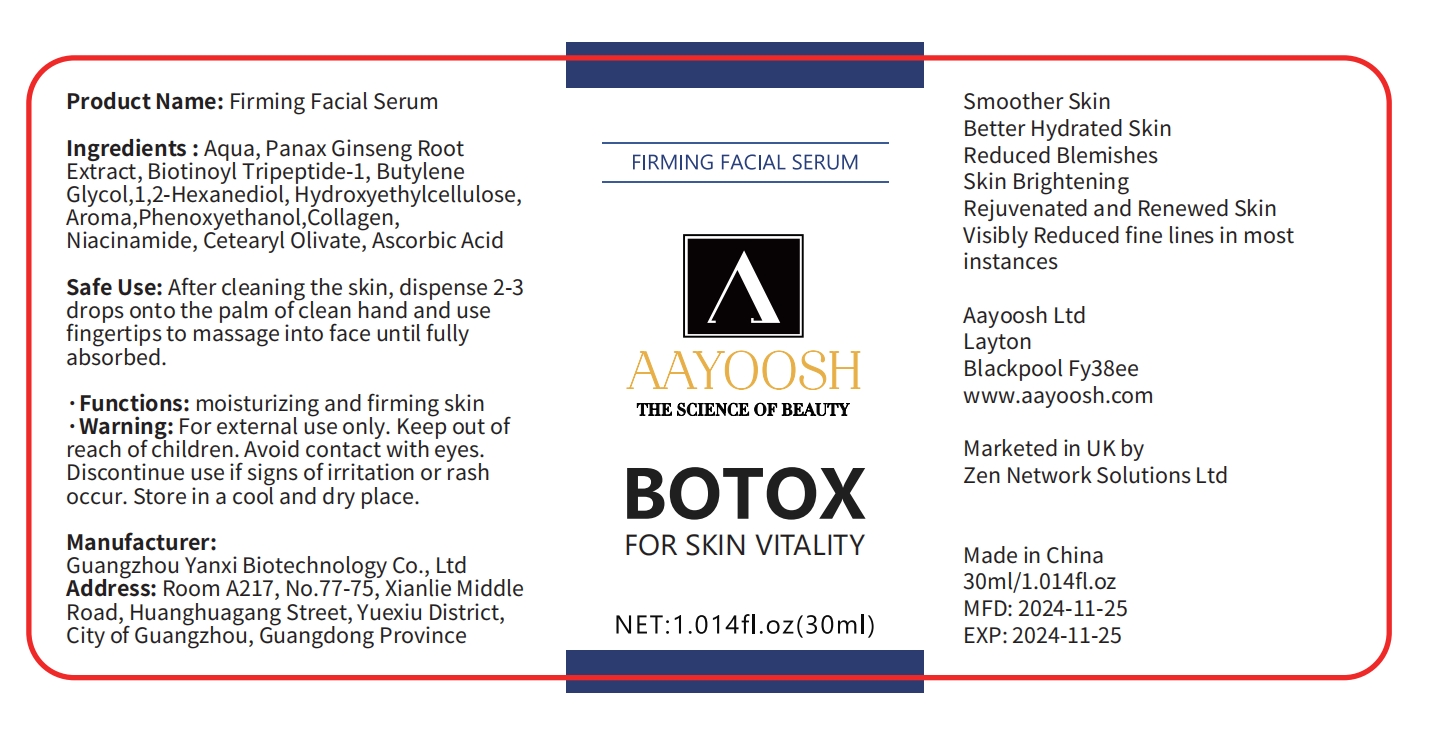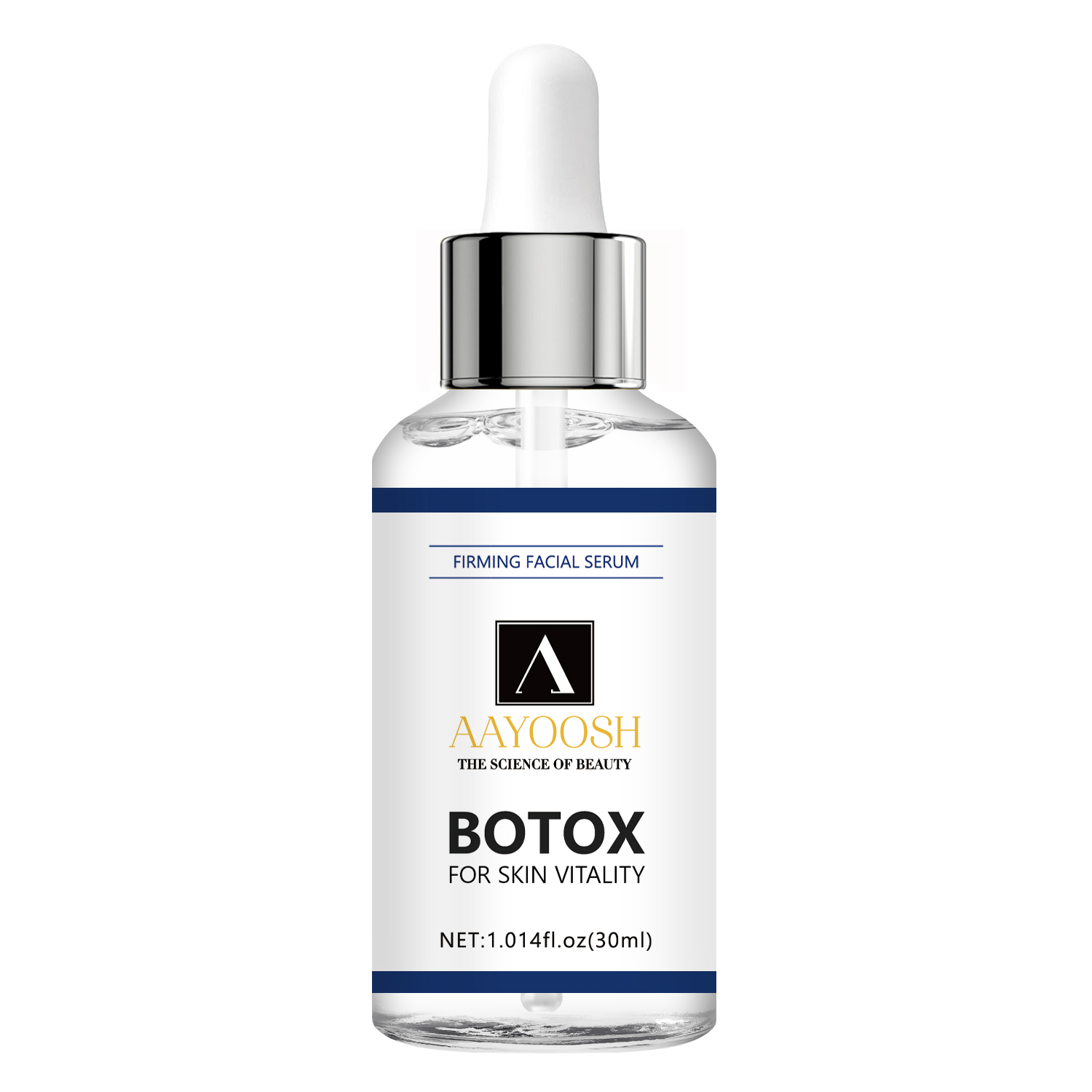 DRUG LABEL: Firming Facial Serum
NDC: 84025-276 | Form: OIL
Manufacturer: Guangzhou Yanxi Biotechnology Co., Ltd
Category: otc | Type: HUMAN OTC DRUG LABEL
Date: 20241127

ACTIVE INGREDIENTS: BIOTINOYL TRIPEPTIDE-1 5 mg/100 mL; BUTYLENE GLYCOL 3 mg/100 mL
INACTIVE INGREDIENTS: WATER

DOSAGE AND ADMINISTRATION

after cleaning the skin, dispense 2-3 drops onto the palm of clean hand and use fingertips to massage into face until fullyabsorbed.

WARNINGS

keep out of children

INACTIVE INGREDIENT

Aqua

INDICATIONS AND USAGE

for daily face care

keep out of children

PURPOSE

moisturizing and firming skin